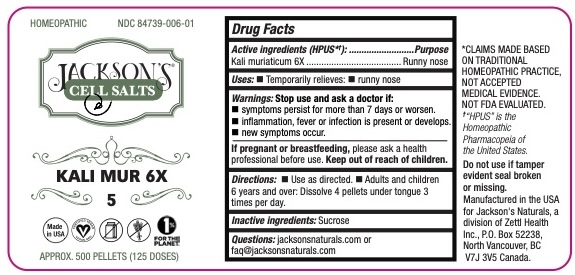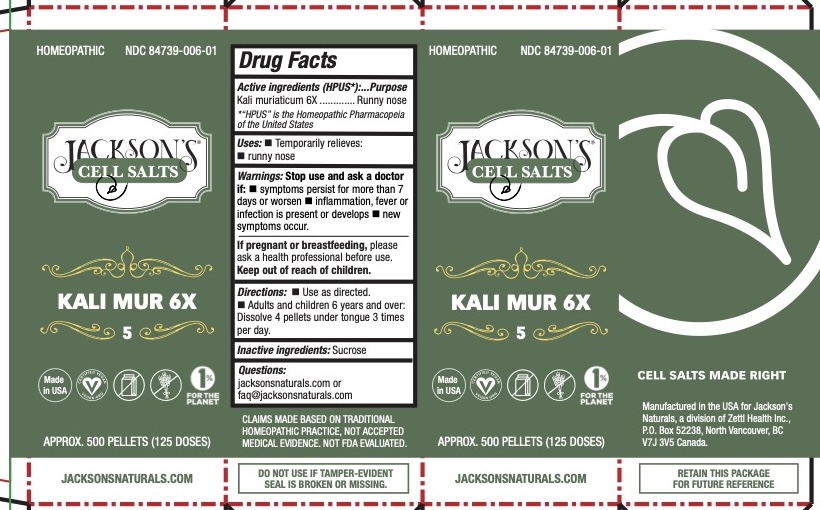 DRUG LABEL: Jacksons Cell Salts KALI MUR 6X
NDC: 84739-006 | Form: PELLET
Manufacturer: Zettl Health Inc.
Category: homeopathic | Type: HUMAN OTC DRUG LABEL
Date: 20251024

ACTIVE INGREDIENTS: SODIUM CHLORIDE 6 [hp_X]/6 [hp_X]
INACTIVE INGREDIENTS: SUCROSE

Jacksons Cell Salts KALI MUR 6X

Active Ingredients

Kali muriaticum 6X

Purpose

Kali muriaticum 6X -- Runny nose

Uses

Temporarily relieves:

• Runny nose

Warnings

Stop use and ask a doctor if:

- symptoms persist for more than 72 hours or worsen
- new symptoms occur

If pregnant or breast-feeding ask a health professional before use. Keep out of reach of children.

Keep out of reach of children

*CLAIMS MADE BASED ON TRADITIONAL HOMEOPATHIC PRACTICE, NOT ACCEPTED MEDICAL EVIDENCE. NOT FDA EVALUATED.

†“HPUS” is the Homeopathic Pharmacopeia of the United States.

Do not use if tamper evident seal broken or missing.

Manufactured in the USA for Jackson's Naturals, a division of Zettl Health Inc., P.O. Box 52238, North Vancouver, BC V7J 3V5 Canada.

Inactive Ingredients

Sucrose

Directions

- Use as directed.
- Adults and children 6 years and over: Dissolve 4 pellets under tongue 3 times per day.

Questions:

jacksonsnaturals.com or

faq@jacksonsnaturals.com